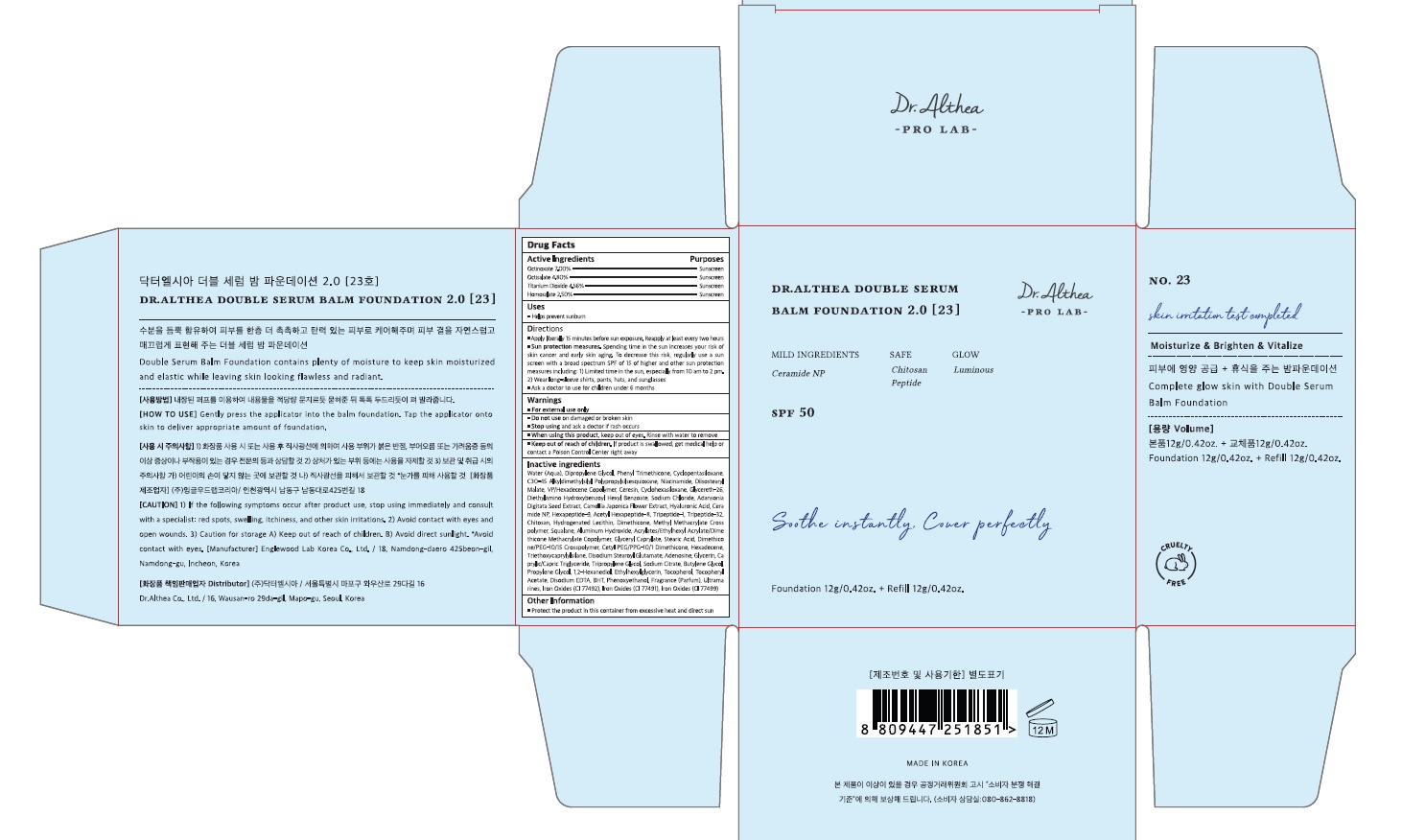 DRUG LABEL: Dr.Althea Double Serum Balm Foundation 23
NDC: 70905-0019 | Form: CREAM
Manufacturer: Dr.Althea Co.,Ltd
Category: otc | Type: HUMAN OTC DRUG LABEL
Date: 20211208

ACTIVE INGREDIENTS: TITANIUM DIOXIDE 4.56 g/100 g; HOMOSALATE 2.5 g/100 g; OCTINOXATE 7 g/100 g; OCTISALATE 4.8 g/100 g
INACTIVE INGREDIENTS: WATER; PHENYL TRIMETHICONE; DIPROPYLENE GLYCOL; CYCLOMETHICONE 5; NIACINAMIDE; VINYLPYRROLIDONE/HEXADECENE COPOLYMER; CERESIN; CYCLOMETHICONE 6; GLYCERETH-26; DIISOSTEARYL MALATE; FERRIC OXIDE YELLOW; DIETHYLAMINO HYDROXYBENZOYL HEXYL BENZOATE; SODIUM CHLORIDE; DIMETHICONE; SQUALANE; METHYL METHACRYLATE/GLYCOL DIMETHACRYLATE CROSSPOLYMER; PHENOXYETHANOL; ALUMINUM HYDROXIDE; GLYCERYL MONOCAPRYLATE; FERRIC OXIDE RED; STEARIC ACID; DIMETHICONE/PEG-10/15 CROSSPOLYMER; CETYL PEG/PPG-10/1 DIMETHICONE (HLB 2); HEXADECENE (MIXED ISOMERS); FERROSOFERRIC OXIDE; TRIETHOXYCAPRYLYLSILANE; ETHYLHEXYLGLYCERIN

70905-0019_Dr.Althea Double Serum Balm Foundation 23

ACTIVE INGREDIENT

Octinoxate 7.00%

Octisalate 4.80%

Titanium Dioxide 4.56%

Homosalate 2.50%

PURPOSE

Sunscreen

INDICATIONS AND USAGE

Helps prevent sunburn

DOSAGE AND ADMINISTRATION

Apply liberally 15 minutes before sun exposure. Reapply at least every two hours

Sun protection measures. Spending time in the sun increases your risk of skin cancer and early skin aging. To decrease this risk, regularly use a sunscreen with a broad spectrum SPF of 15 of higher and other sun protection measures including: 1) Limited time in the sun, especially from 10 am to 2 pm. 2) Wear long-sleeve shirts, pants, hats, and sunglasses

Ask a doctor to use for children under 6 months

WARNINGS

For external use only

Do not use on damaged or broken skin

When using this product, keep out of eyes. Rinse with water to remove.

Stop using and ask a doctor if rash occurs.

KEEP OUT OF REACH OF CHILDREN

Keep out of reach of the children. If product is swallowed, get medical help or contact a poison control center right away.

INACTIVE INGREDIENT

Water (Aqua), Dipropylene Glycol, Phenyl Trimethicone, Cyclopentasiloxane, C30-45 Alkyldimethylsilyl Polypropylsilsesquioxane, Niacinamide, Diisostearyl Malate, VP/Hexadecene Copolymer, Ceresin, Cyclohexasiloxane, Glycereth-26, Diethylamino Hydroxybenzoyl Hexyl Benzoate, Sodium Chloride, Adansonia Digitata Seed Extract, Camellia Japonica Flower Extract, Hyaluronic Acid, Ceramide NP, Hexapeptide-9, Acetyl Hexapeptide-8, Tripeptide-1, Tripeptide-32, Chitosan, Hydrogenated Lecithin, Dimethicone, Methyl Methacrylate Crosspolymer, Squalane, Aluminum Hydroxide, Acrylates/Ethylhexyl Acrylate/Dimethicone Methacrylate Copolymer, Glyceryl Caprylate, Stearic Acid, Dimethicone/PEG-10/15 Crosspolymer, Cetyl PEG/PPG-10/1 Dimethicone, Hexadecene, Triethoxycaprylylsilane, Disodium Stearoyl Glutamate, Adenosine, Glycerin, Caprylic/Capric Triglyceride, Tripropylene Glycol, Sodium Citrate, Butylene Glycol, Propylene Glycol, 1,2-Hexanediol, Ethylhexylglycerin, Tocopherol, Tocopheryl Acetate, Disodium EDTA, BHT, Phenoxyethanol, Fragrance (Parfum), Ultramarines, Iron Oxides (CI 77492), Iron Oxides (CI 77491), Iron Oxides (CI 77499)

OTHER SAFETY INFORMATION

Protect the product in the container from excessive heat and direct sun